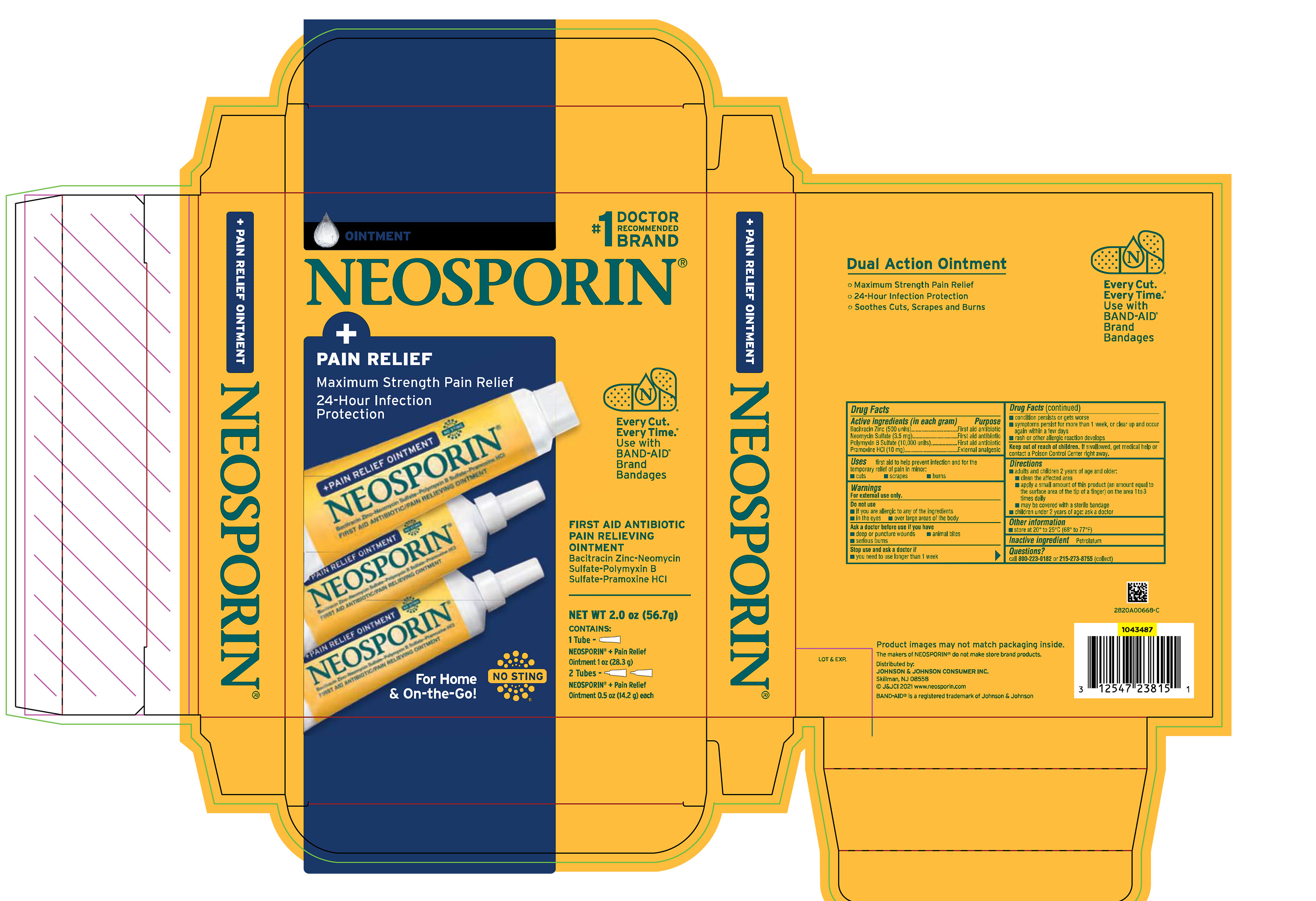 DRUG LABEL: Neosporin Plus Pain Relief
NDC: 69968-0801 | Form: KIT | Route: TOPICAL
Manufacturer: Kenvue Brands LLC
Category: otc | Type: HUMAN OTC DRUG LABEL
Date: 20241114

ACTIVE INGREDIENTS: NEOMYCIN SULFATE 3.5 mg/1 g; POLYMYXIN B SULFATE 10000 [USP'U]/1 g; PRAMOXINE HYDROCHLORIDE 10 mg/1 g; BACITRACIN ZINC 500 [USP'U]/1 g; NEOMYCIN SULFATE 3.5 mg/1 g; POLYMYXIN B SULFATE 10000 [USP'U]/1 g; PRAMOXINE HYDROCHLORIDE 10 mg/1 g; BACITRACIN ZINC 500 [USP'U]/1 g
INACTIVE INGREDIENTS: PETROLATUM; PETROLATUM

Neosporin Plus Pain Relief Clubtray

Drug Facts

ACTIVE INGREDIENT

Active ingredients (in each gram) | Purpose
Bacitracin Zinc (500 units) | First aid antibiotic
Neomycin Sulfate (3.5 mg) | First aid antibiotic
Polymyxin B Sulfate (10,000 units) | First aid antibiotic
Pramoxine HCl (10 mg) | External analgesic

Uses

first aid to help prevent infection and for the temporary relief of pain in minor:

- cuts
- scrapes
- burns

Warnings

For external use only.

Do not use

- if you are allergic to any of the ingredients
- in the eyes
- over large areas of the body

Ask a doctor before use if you have

- deep or puncture wounds
- animal bites
- serious burns

Stop use and ask a doctor if

- you need to use longer than 1 week
- condition persists or gets worse
- symptoms persist for more than 1 week, or clear up and occur again within a few days
- rash or other allergic reaction develops

Keep out of reach of children.

If swallowed, get medical help or contact a Poison Control Centre right away.

Directions

- adults and children 2 years of age and older:
  - clean the affected area
  - apply a small amount of this product (an amount equal to the surface area of the tip of a finger) on the area 1 to 3 times daily
  - may be covered with a sterile bandage
- children under 2 years of age: ask a doctor

Other information

- store at 20° to 25°C (68° to 77°F)

Inactive ingredients

Petrolatum

Questions?

call 800-223-0182 or 215-273-8755 (collect)

Distributed by:
JOHNSON & JOHNSON CONSUMER INC.
Skillman, NJ 08558

PRINCIPAL DISPLAY PANEL - Kit Package Label

#1 DOCTOR

RECOMMENDED

BRAND

OINTMENT

NEOSPORIN®

+

PAIN RELIEF

Maximum Strength Pain Relief

24-Hour Infection

Protection

Every Cut.

Every Time.®

Use with

BAND-AID®

Brand

Bandages

FIRST AID ANTIBIOTIC

PAIN RELIEVING

OINTMENT

Bacitracin Zinc-Neomycin

Sulfate-Polymyxin B

Sulfate-Pramoxine HCl

For Home

& On-the-Go!

NO STING

NEW WT 2.0 oz (56.7g)

CONTAINS:

1 Tube -

NEOSPORIN® + Pain Relief

Ointment 1 oz (28.3 g)

2 Tubes –

NEOSPORIN® + Pain Relief

Ointment 0.5 oz (14.2 g) each